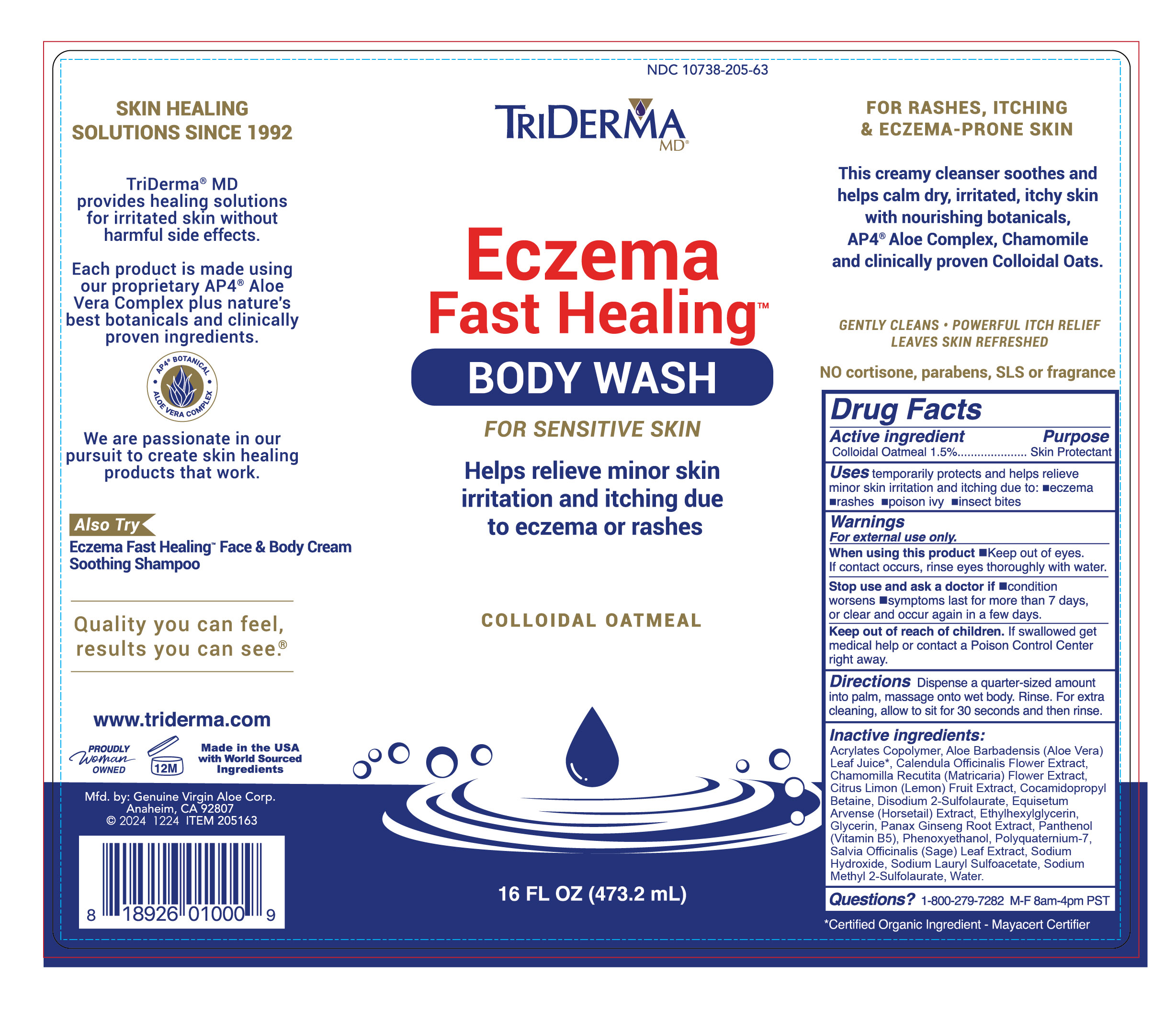 DRUG LABEL: Eczema Fast Healing Body Wash
NDC: 10738-205 | Form: LOTION/SHAMPOO
Manufacturer: Genuine Virgin Aloe Corporation
Category: otc | Type: HUMAN OTC DRUG LABEL
Date: 20260124

ACTIVE INGREDIENTS: OATMEAL 15 mg/1 mL
INACTIVE INGREDIENTS: PHENOXYETHANOL; SODIUM LAURYL SULFOACETATE; PANTHENOL; SODIUM METHYL 2-SULFOLAURATE; EQUISETUM ARVENSE STEM OIL; CITRUS LIMON (LEMON) FRUIT OIL; POLYQUATERNIUM-7; DISODIUM 2-SULFOLAURATE; PANAX GINSENG ROOT OIL; CHAMOMILE FLOWER OIL; CALENDULA OFFICINALIS FLOWER; COCAMIDOPROPYL BETAINE; SALVIA OFFICINALIS ROOT; SODIUM HYDROXIDE; GLYCERIN; ALOE VERA LEAF; WATER; ETHYLHEXYLGLYCERIN

TriDerma Eczema Fast Heaing Body Wash

Active Ingredient

Colloidal Oatmeal 1.5%

Purpose

Skin Protectant

Uses

Temporarily protects and helps relieve minor skin irritation and itching due to: •eczema •rashes •poison ivy •insect bites

Warnings

For external use only

When using this product • Keep out of eyes. If contact occurs, rinse eyes thoroughly with water.

Stop use and ask a doctor if • condition worsens • symptoms last for more than 7 days, or clear and occur again in a few days

Do not use • on deep puncture wounds • on animals • on bites • on serious burns

Keep out of reach of children. If swallowed get medical help or contact a Poison Control Center right away.

Directions

Dispense a quarter-sized amount into palm, gently massage onto wet skin. Rinse. For extra cleansing, allow to sit for 30 seconds and then rinse.

Ingredients

Acrylates Copolymer, Aloe Barbadensis (Aloe Vera) Leaf Juice*, Calendula Officinalis Flower Extract, Chamomilla Recutita (Matricaria) Flower Extract, Citrus Limon (Lemon) Fruit Extract, Cocamidopropyl Betaine, Disodium 2-Sulfolaurate, Equisetum Arvense (Horsetail) Extract, Ethylhexylglycerin, Glycerin, Panax Ginseng Root Extract, Panthenol (Vitamin B5), Phenoxyethanol, Polyquaternium-7, Salvia Officinalis (Sage) Leaf Extract, Sodium Hydroxide, Sodium Lauryl Sulfoacetate, Sodium Methyl 2-Sulfolaurate, Water.

*Certified Organic Ingredient - Mayacert Certifier

Questions?

1-800-279-7282 M-F 8am-4pm PST

PACKAGE LABEL

Triderma MD

Eczema Fast HealingTM Body Wash

For Sensitive Skin

Helps relieve minor skin irritation & itching due to eczema & rashes

Colloidal Oatmeal

16 Fl OZ (473 mL)